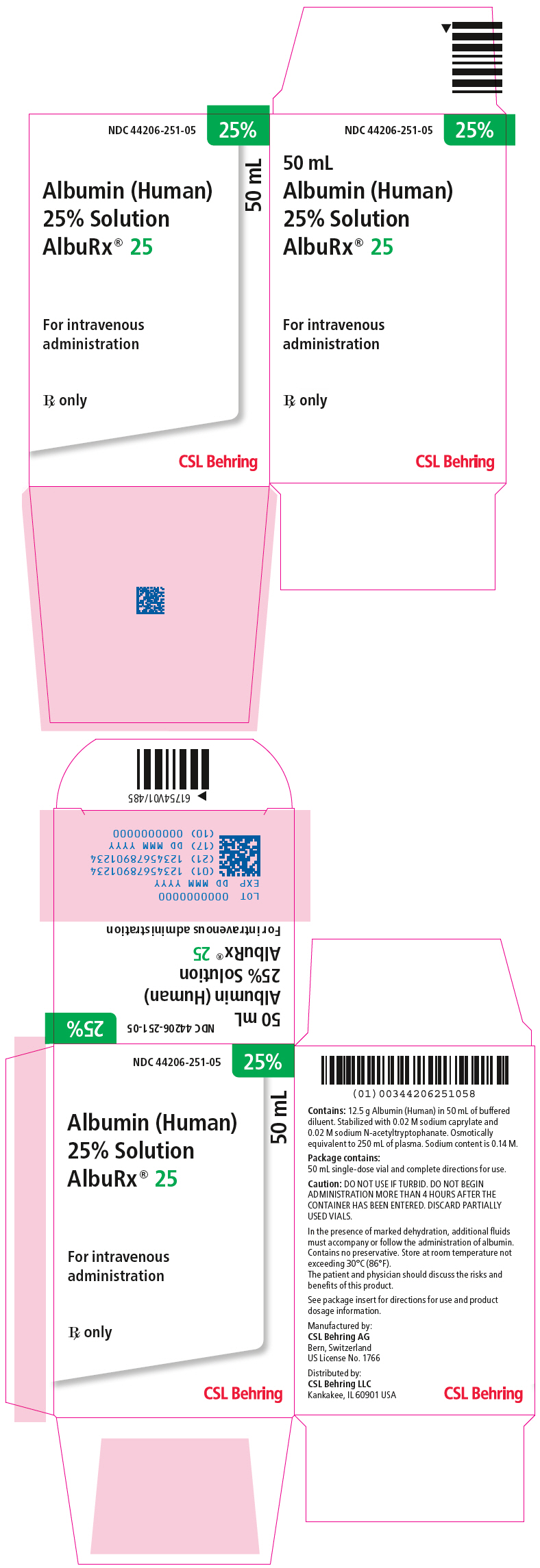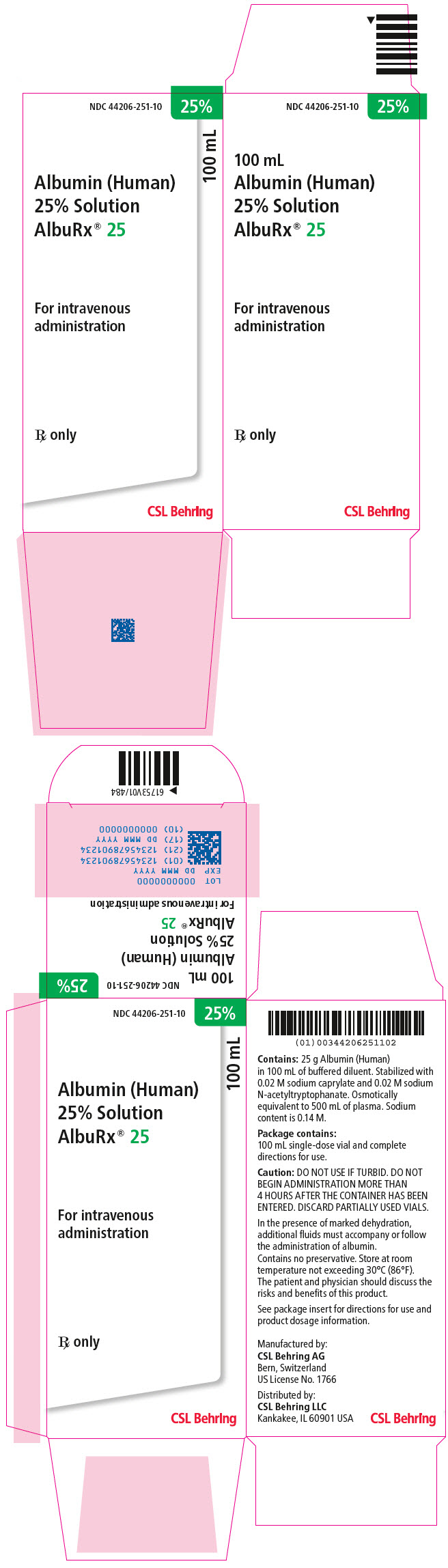 DRUG LABEL: AlbuRx
NDC: 44206-251 | Form: SOLUTION
Manufacturer: CSL Behring AG
Category: other | Type: PLASMA DERIVATIVE
Date: 20220804

ACTIVE INGREDIENTS: ALBUMIN HUMAN 12.5 g/50 mL
INACTIVE INGREDIENTS: SODIUM CHLORIDE; POTASSIUM CHLORIDE; N-ACETYL-DL-TRYPTOPHAN SODIUM; Sodium caprylate

Albumin (Human) 25% Solution
ALBURX® 25

RX only

DESCRIPTION

ALBURX® 25, Albumin (Human) 25% solution is a sterile aqueous solution for intravenous administration containing the albumin component of human blood. The solution is clear and slightly viscous; it is almost colorless, or yellow, amber, or green.

This product is prepared from the plasma of US donors. The product has been produced by alcohol fractionation and has been heated for 10 hours at 60°C for inactivation of infectious agents. The results of virus validation studies have shown that the manufacturing process, particularly alcohol fractionation, eliminates enveloped and non-enveloped viruses. Additionally, heat treatment at 60°C for a period of 10 hours efficiently inactivates viruses. The solution contains 0.14 M (3.2 mg/mL) sodium. The aluminum content is ≤ 200 mcg/L and the potassium content is ≤ 0.002 M. The solution is stabilized with 0.02 M sodium N-acetyltryptophanate and 0.02 M sodium caprylate. The solution contains no preservative.

CLINICAL PHARMACOLOGY^13,17

ALBURX® 25, Albumin (Human) 25% solution should not be used as an intravenous nutrient because of the slow breakdown and relatively unfavorable composition of the albumin molecule with respect to its content of essential amino acids. Oral provision of proteins or an intravenous regimen providing adequate calories and a suitable amino acid mixture are the methods of choice for the treatment of protein malnutrition as such, though they do not permit the rapid correction of hypoproteinemia.

The binding properties of albumin may provide an indication for its use in severe hemolytic disease of the newborn, where it may lower the plasma concentration of free bilirubin pending an exchange transfusion. This effect is possibly also relevant in certain cases of acute liver failure with rapidly increasing levels of serum bilirubin, particularly in the presence of severe hypoproteinemia.

The colloid osmotic or oncotic properties of albumin at this moment constitute the predominant reason for its clinical use. The rationale for this is the Starling concept of the capillary balance of hydrostatic and oncotic pressure gradients across the capillary walls as the determinant of the fluid – i.e. volume – distribution between the intravascular and the interstitial compartment.^16 The two main indications for the use of ALBURX® 25, Albumin (Human) 25% solution are therefore a plasma or blood volume deficit and the oncotic deficit resulting from hypoproteinemia. The 25% concentration is oncotically equivalent to approximately five times its volume of normal human plasma. The effective colloid osmotic pressure of the serum proteins depends very largely on the relatively small and numerous albumin molecules, which therefore play a decisive role in the maintenance of the circulating plasma volume.

INDICATIONS AND USAGE

General Principles^17

Volume Deficit

Since the oncotic pressure of ALBURX® 25, Albumin (Human) 25% solution is about four times higher than that of normal human serum, it will expand the plasma volume if interstitial water is available for an inflow through the capillary walls. However, many patients suffering from an acute volume deficit also have some degree of interstitial dehydration. In the absence of hyperhydration, the treatment of an acute volume deficit with ALBURX® 25 should therefore include isotonic electrolyte solutions with an albumin:electrolyte ratio of 1:3 or 1:4. By contrast, chronic volume deficits have usually been at least partially compensated for by the renal retention of sodium and water with some degree of tissue edema, and in these circumstances a trial with ALBURX® 25 only is indicated. In any case, an anemia of clinically relevant magnitude requires specific treatment, and the metabolic needs of the patient with respect to fluid and electrolytes must be cared for.

Oncotic Deficit

The common causes of hypoproteinemia are protein-calorie malnutrition, defective absorption in gastro-intestinal disorders, faulty albumin synthesis in chronic hepatic failure, increased protein catabolism postoperatively or with sepsis, and abnormal renal losses of albumin with chronic kidney disease. In all these settings, the circulating albumin mass is initially maintained by a gradual transfer of extravascular albumin to the circulation, and hypoproteinemia ensues only when this compensatory potential has been exhausted. This implies that manifest hypoproteinemia is usually accompanied by a hidden extravascular albumin deficit of equal magnitude as the measurable intravascular deficit, which must be allowed for if ALBURX® 25, Albumin (Human) 25% solution is infused because of the capillary permeability of that protein.

The primary sequel of the oncotic deficit resulting from hypoproteinemia is a loss of plasma and a gain of interstitial volume with increased lymphatic flow. As a secondary response, the kidney retains sodium and water which distribute themselves on both sides of the capillary walls and the plasma volume may be returned almost to normal when the interstitial hydrostatic pressure increases sufficiently to compensate for the decrease of the serum oncotic pressure. This chain of events is accelerated by the infusion of crystalloid fluids. The plasma volume is maintained at the price of interstitial edema.^2

There is some evidence that a serum oncotic pressure near 20 mmHg – equaling a total serum protein (TSP) concentration of 5.2 g/100 mL – represents a threshold, below which the risk of complications increases.^17 The target organs of hypoproteinemia include the skin, the lungs, and the intestine.^10 Cutaneous edema lowers the oxygen tension of wounds and may thus impair the healing process.^5 An oncotic deficit favors the development of interstitial pulmonary edema^4 and the intestinal accumulation of fluids, which may progress to a paralytic ileus.^9

Relief of the basic pathology is the definitive mode of therapy for the restoration of the plasma protein content, but this process takes time to become effective, and the rapid correction of a critical oncotic deficit by the administration of ALBURX® 25, Albumin (Human) 25% solution – possibly in conjunction with a diuretic – may therefore be indicated, particularly in high-risk patients who have undergone abdominal, cardiovascular, thoracic, or urologic surgery or who have acute bacteremia. In notably catabolic patients, attempts to raise the TSP level above 6 g/100 mL usually prove futile, even with massive doses of Albumin (Human).^17

It is emphasized that whereas ALBURX® 25, Albumin (Human) 25% solution may be necessary to prevent or treat the aforementioned acute complications of hypoproteinemia, it is not indicated for treatment of the chronic condition itself.

Specific Indications^17

Acute circumstances in which ALBURX® 25, Albumin (Human) 25% solution use is usually appropriate

Shock

Though electrolyte solutions such as Ringer's lactate and colloid-containing plasma substitutes may be used as an emergency treatment of shock, ALBURX® 25, Albumin (Human) 25% solution used according to the aforementioned principles has a much longer intravascular half-life and may therefore be preferable. In addition, anemia of clinically relevant magnitude requires specific therapy with red cells.

Burns

Immediate therapy during the first 24 hours is directed at the administration of large volumes of crystalloid solutions and lesser amounts of ALBURX® 25, Albumin (Human) 25% solution to maintain an adequate plasma volume and protein (colloid) content. For continuation of therapy beyond 24 hours, larger amounts of ALBURX® 25 and lesser amounts of crystalloid are generally used.^17 An optimum regimen for the use of Albumin (Human), electrolytes, and fluid in the early treatment of burns has, however, not yet been established.

With restoration of normal capillary function, a close relationship exists once again between infused Albumin (Human) and resultant increase in plasma oncotic pressure. A goal should be sought of maintaining a plasma albumin concentration of about 2.5 ±0.5 g/100 mL or a plasma oncotic pressure of 20 mmHg (equivalent to a TSP concentration of 5.2 g/100 mL).^17 In the presence of extensive granulating wounds, a daily loss of up to 30 g of albumin may continue into the late post-burn period.^1 Protein-rich oral feedings, or adequate parenteral nutrition should be included in the overall regimen to the fullest possible extent, though such treatment does not permit the rapid correction of an oncotic deficit.

Acute circumstances in which ALBURX® 25, Albumin (Human) 25% solution use may be appropriate

Adult Respiratory Distress Syndrome

Several factors are usually involved in the development of the state now commonly called the adult respiratory distress syndrome, one of these being a hypoproteinemic fluid overload. If present, this may be corrected by the use of ALBURX® 25, Albumin (Human) 25% solution and a diuretic.^14,17

Cardiopulmonary Bypass

An adequate blood volume during cardiopulmonary bypass can be maintained with crystalloids as the only pump priming fluid, but only at the price of interstitial edema. A commonly employed program is an ALBURX® 25, Albumin (Human) 25% solution and crystalloid pump prime adjusted so as to achieve a hematocrit of 20% and a plasma albumin level of 2.5 g/100 mL in the patient, but the level to which either may be lowered safely has not yet been defined.^17

Pre- and postoperative Hypoproteinemia

Patients undergoing major surgery may lose more than half of their circulating albumin mass^6,9,15, and complications attributable to an oncotic deficit may occur in such cases, as well as in septic and intensive care patients. Oncotic therapy with ALBURX® 25, Albumin (Human) 25% solution may therefore be indicated in such patients, according to the principles outlined in Oncotic Deficit. Temporary redistribution of protein is usually not an indication for Albumin (Human).

Third Space Problems of Infectious Origin

The sequestration of protein-rich fluid during acute peritonitis, pancreatitis, mediastinitis or extensive cellulitis may be of sufficient magnitude to require the treatment of a volume or an oncotic deficit with ALBURX® 25, Albumin (Human) 25% solution^3, although this occurrence is relatively rare.

Acute Liver Failure

In acute liver failure, ALBURX® 25, Albumin (Human) 25% solution may serve the triple purpose of stabilizing the circulation, correcting an oncotic deficit and binding excessive serum bilirubin. The therapeutic approach is guided by the individual circumstances.^17

Acute Nephrosis

Patients with acute nephrosis may prove refractory to cyclophosphamide or steroid therapy and their edema may even be aggravated initially by steroids. In such cases, a response may be elicited by combining 100 mL of 20–25% Albumin (Human) solution with an appropriate diuretic. This combination should be repeated daily for about one week, after which the patient may react satisfactorily to drug therapy.^17

Ascites

The use of ALBURX® 25, Albumin (Human) 25% solution for blood volume support may be indicated if circulatory instability follows the withdrawal of ascitic fluid.

Red Cell Resuspension Media

As a rule, the use of Albumin (Human) for resuspending red cells can be dispensed with. However, in exceptional circumstances such as certain types of exchange transfusions and the use of very large volumes of erythrocyte concentrates and frozen or washed red cells, the addition of ALBURX® 25, Albumin (Human) 25% solution to the resuspension medium may be indicated in order to provide sufficient volume and/or avoid excessive hypoproteinemia during the subsequent transfusion. If necessary, 20–25 g or more of Albumin (Human) per liter of red cell suspension should be added as a concentrated solution to the isotonic, electrolyte suspension of erythrocytes immediately before transfusion, the individual dosage depending on the TSP level of the recipient.

Renal Dialysis

Patients undergoing long-term hemodialysis may need ALBURX® 25, Albumin (Human) 25% solution for the treatment of a volume or an oncotic deficit. As a rule, the initial dose should not exceed 100 mL of a 20–25% solution, and the patients should be carefully observed for signs of a circulatory overload, to which they are particularly sensitive.

Hemolytic Disease of the Newborn

ALBURX® 25, Albumin (Human) 25% solution may be indicated in order to bind and thus detoxify free serum bilirubin in severely hemolytic infants pending an exchange transfusion.

Circumstances in which ALBURX® 25, Albumin (Human) 25% solution use is not justified

For the reasons set forth in sections CLINICAL PHARMACOLOGY. and General Principles, there is no valid reason for the use of ALBURX® 25, Albumin (Human) 25% solution as an intravenous nutrient or for treating the stabilized hypoproteinemia accompanying chronic cirrhosis, chronic nephrosis, protein-losing enteropathy, malabsorption and pancreatic insufficiency.

If, however, a patient in this category has to cope with a superimposed acute stress, e.g. anesthesia, surgery or major infections, the patient's hemodynamic state, oncotic deficit and fluid balance should be carefully assessed and the appropriate steps taken as indicated by the individual circumstances.

CONTRAINDICATIONS

The only specific contraindication to the use of ALBURX® 25, Albumin (Human) 25% solution is a history of an incompatibility reaction to Albumin (Human) in the individual recipient (see ADVERSE REACTIONS).

WARNINGS

ALBURX® 25, Albumin (Human) 25% solution is made from human plasma. Products made from human plasma may contain infectious agents, such as viruses, that can cause disease. The risk that such products will transmit an infectious agent has been extremely reduced by screening plasma donors for prior exposure to certain viruses, by testing for the presence of certain current virus infections, and by inactivating and/or removing certain viruses through alcohol fractionation and through heat treatment of the product in the final container for 10 hours at 60°C. Despite these measures, such products can still potentially transmit disease. A theoretical risk for transmission of Creutzfeldt-Jakob Disease (CJD) is considered extremely remote. No cases of transmission of viral diseases or CJD have ever been identified for Albumin (Human). There is also the possibility that unknown infectious agents may be present in such products. All infections thought by a physician possibly to have been transmitted by this product should be reported by the physician or other healthcare provider to CSL Behring Pharmacovigilance Department at 1-866-915-6958. The physician should discuss the risks and benefits of this product with the patient.

Turbid solutions must not be used. Do not begin administration more than 4 hours after introduction of the administration set. Partially used bottles must be discarded. There exists a risk of potentially fatal hemolysis and acute renal failure from the inappropriate use of sterile water for injection as a diluent for ALBURX® 25, Albumin (Human) 25% solution. Acceptable diluents include 0.9% sodium chloride or 5% dextrose in water.

PRECAUTIONS

Adequate precautions should be taken against circulatory overload and may include pulmonary auscultation or X-ray as well as monitoring the central venous or pulmonary artery wedge pressure. Special caution is indicated in patients with stabilized chronic anemia, congestive heart failure and renal insufficiency.

Pregnancy

Animal reproduction studies have not been conducted with ALBURX® 25, Albumin (Human) 25% solution. It is also not known whether ALBURX® 25 can cause fetal harm when administered to a pregnant woman or can affect reproduction capacity. ALBURX® 25 should be given to a pregnant woman only if clearly needed. There is, however, no evidence for any contraindication to the use of ALBURX® 25 specifically associated with reproduction, pregnancy or the fetus.

Use an intravenous infusion set suitable for the infusion of blood and blood products.

ADVERSE REACTIONS

Since ALBURX® 25, Albumin (Human) 25% solution is sterile when coming from the manufacturer, bacterial contamination with the risk of post-infusion septicemia can only occur if the container has been damaged or following puncture of the rubber cap (see WARNINGS).

Though very rare, non-septic incompatibility reactions including nausea, chills, fever, urticaria, headache and hypotension following the administration of albumin-containing preparations have been recorded.^8,11,12,17 A favorable response was observed to the intravenous administration of 50 to 100 mg of prednisolone.^12 Severe allergic reactions such as anaphylactic shock have been reported.

DOSAGE AND ADMINISTRATION

ALBURX® 25, Albumin (Human) 25% solution must be administered intravenously. The venipuncture site should not be infected or traumatized, and should be prepared with standard aseptic technique. The solution is compatible with whole blood or packed red cells as well as the usual electrolyte and carbohydrate solutions intended for intravenous use. By contrast, it should not be mixed with protein hydrolysates, amino acid mixtures, or solutions containing alcohol. It is ready for use as contained in the bottle and may be given without regard to the blood group of the recipient.

The dosage of ALBURX® 25, Albumin (Human) 25% solution is based on the principles outlined in the section on INDICATIONS AND USAGE but should always be adapted to the individual situation. The quantities required may be underestimated because of hidden extravascular deficits, and the effect of ALBURX® 25 infusion on the serum protein level should therefore be checked by laboratory analysis.

Volume Deficit

The appropriate ALBURX® 25, Albumin (Human) 25% solution dose for the treatment of a volume deficit should be estimated from the recipient's hemodynamic response^7, supplemented with the established safeguards against a circulatory overload. In the absence of active hemorrhage, the total dose should at any rate not exceed the normal circulating albumin mass, i.e. 2 g per kg body weight.

Oncotic Deficit

The appropriate ALBURX® 25, Albumin (Human) 25% solution dose in grams of protein for the correction of an oncotic deficit can, as an average, be estimated from the difference between the desired and the actual TSP level x plasma volume (~40 mL/kg) × 2, the latter factor allowing for the hidden extravascular deficit. The individual effect is, however, variable and should be checked by measuring the post-infusion TSP level.^10,17

Hemolytic Disease of the Newborn

The appropriate ALBURX® 25, Albumin (Human) 25% solution dose for the binding of free serum bilirubin in severely hemolytic infants is 1 g/kg body weight, to be given about one hour prior to the exchange transfusion, and caution is recommended in hypervolemic infants.

ALBURX® 25, Albumin (Human) 25% solution is clear and slightly viscous; it is almost colorless, or yellow, amber, or green. Parenteral drug products should be inspected visually for particulate matter and discoloration prior to administration, whenever solution and container permit. Do not use solution that is turbid or contains particulate matter.

HOW SUPPLIED

ALBURX® 25 is supplied as a 25% solution (250 g/L).

Each product presentation includes a package insert and the components listed in Table 1 below.

Table 1. How Supplied
Presentation | Carton NDC Number | Components
50 mL | 44206-251-05 | One single-dose vial containing 12.5 grams of albumin [NDC 44206-251-90]
100 mL | 44206-251-10 | One single-dose vial containing 25 grams of albumin [NDC 44206-251-91]

STORAGE

ALBURX® 25, Albumin (Human) 25% solution should be stored at a temperature not exceeding 30°C (86°F). It should not be used after the expiration date printed on the label.

REFERENCES

1. Birke G, Liljedahl SO, Plantin LO, Reizenstein P. Acta Chir. Scand. 1968;134:27.
2. Cervera AL, Moss G. J. Trauma. 1974;14:506.
3. Clowes GH Jr, Vucinic M, Weidner MG. Ann. Surg. 1966;163:866.
4. Gaar KA Jr, Taylor AE, Owens LJ, Guyton AC. Amer. J. Physiol. 1967;213:79.
5. Heughan C, Niinikoski J, Hunt TK. Surg. Gynec. Obstet. 1972;135:257.
6. Hoye RC, Paulson DF, Ketcham AS. Surg. Gynec. Obstet. 1970;131:943.
7. Kinney JM, Egdahl RH, Zuidema GD. Manual of Preoperative and Postoperative Care, American College of Surgeons. Philadelphia: W. B. Saunders Co; 1971.
8. Lowenstein E. In: Sgouris JT, René A, ed. Proceedings of the Workshop on Albumin, February 12–13. Bethesda, Maryland 20014: DHEW Publication NIH 76-925, NHLI; p. 302, 1975.
9. Moss G. Surg. Forum. 1967;18:333.
10. Pappova E, Bachmeier W, Crevoisier JL, Kollar J, Kollar M, Tobler P, Zahler HW, Zaugg D, Lundsgaard-Hansen P. Vox Sang. 1977;33:307.
11. Ring J, Messmer K. Lancet. 1977;1:466.
12. Ring J, Seifert J, Lob G, Coulin K, Brendel W. Klin. Wschr. 1974;52:595.
13. Sgouris JT, René A, ed. Proceedings of the Workshop on Albumin, February 12–13. Bethesda, Maryland 20014: DHEW Publication NIH 76-925, NHLI; 1975.
14. Skillman JJ, Parikh BM, Tanenbaum BJ. Amer. J. Surg. 1970;119:440.
15. Skillman JJ, Tanenbaum BJ. Current Topics in Surgical Research. New York: Academic Press; 1970;2:523.
16. Starling EH. J. Physiol. 1896;19:312-326.
17. Tullis JL. JAMA. 1977;237:355,460.

Manufactured by:
CSL Behring AG
Bern, Switzerland
US License No. 1766

Distributed by:
CSL Behring LLC
Kankakee, IL 60901 USA

Revised: July 2022

Principal Display Panel - 50 mL Vial Carton

NDC 44206-251-05
25%

50 mL
Albumin (Human)
25% Solution
AlbuRx® 25

For intravenous
administration

Rx only

CSL Behring

Principal Display Panel - 100 mL Vial Carton

NDC 44206-251-10
25%

100 mL
Albumin (Human)
25% Solution
AlbuRx® 25

For intravenous
administration

Rx only

CSL Behring